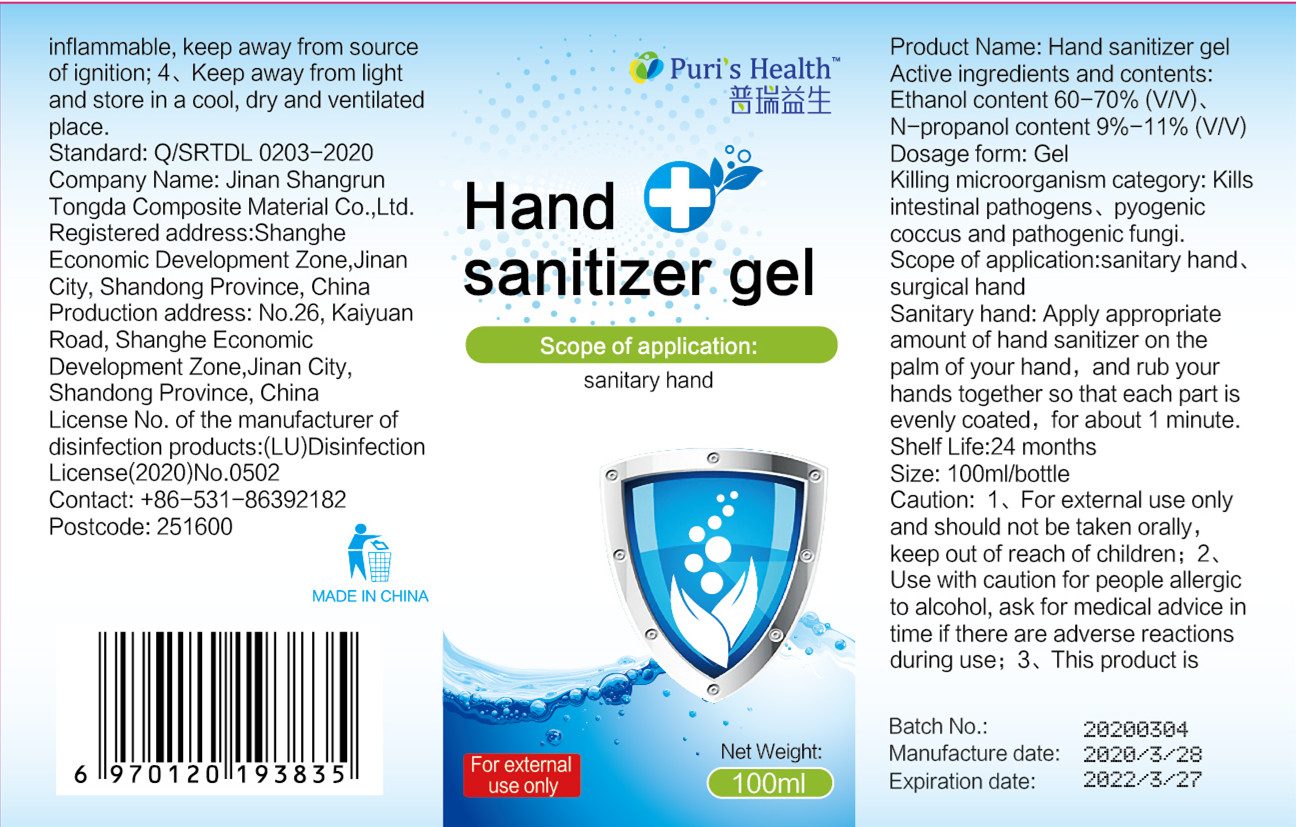 DRUG LABEL: Hand Sanitizer Gel
NDC: 52998-001 | Form: GEL
Manufacturer: Jinan Shangrun Tongda Composite Material Co., Ltd.
Category: otc | Type: HUMAN OTC DRUG LABEL
Date: 20200429

ACTIVE INGREDIENTS: ALCOHOL 78 mL/100 mL
INACTIVE INGREDIENTS: WATER; TROLAMINE; GLYCERIN

DOSAGE AND ADMINISTRATION

Keep away from lightand store in a cool, dry and ventilated place.

INACTIVE INGREDIENT

Triethanolamine

glycerin

SF-1

water

INDICATIONS AND USAGE

Apply appropriate amount of hand sanitizer on the palm of your hand, and rub your hands together so that each part is evenly coated, for about 1 minute.

ACTIVE INGREDIENT

Absolute ethanol

keep out of reach of children

PURPOSE

Disinfection
Sterilization
No Rinseing

WARNINGS

1、For external use only and should not be taken orally,keep out of reach of children;

2、Use with caution for people allergic to alcohol, ask for medical advice in time if there are adverse reactionsduring use;

3、This product is inflammable, keep away from source of ignition;

4、Keep away from light and store in a cool, dry and ventilated place.